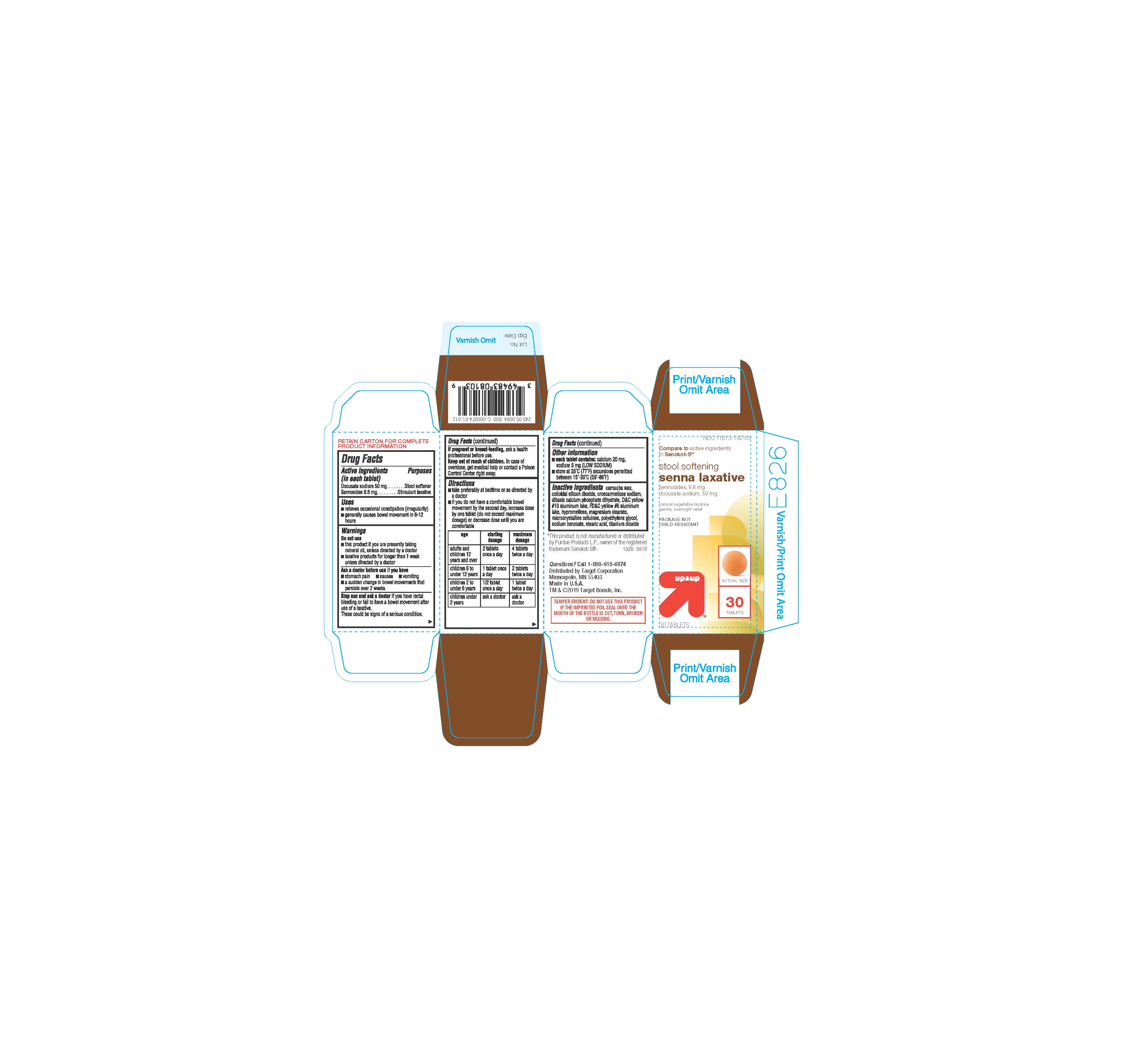 DRUG LABEL: STOOL SOFTENING SENNA LAXATIVE
NDC: 11673-192 | Form: TABLET
Manufacturer: TARGET CORPORATION
Category: otc | Type: HUMAN OTC DRUG LABEL
Date: 20190228

ACTIVE INGREDIENTS: DOCUSATE SODIUM 50 mg/1 1; SENNOSIDES A AND B 8.6 mg/1 1
INACTIVE INGREDIENTS: SODIUM BENZOATE; TITANIUM DIOXIDE; HYPROMELLOSES; MAGNESIUM STEARATE; MICROCRYSTALLINE CELLULOSE; CARNAUBA WAX; SILICON DIOXIDE; DIBASIC CALCIUM PHOSPHATE DIHYDRATE; D&C YELLOW NO. 10; FD&C YELLOW NO. 6; POLYETHYLENE GLYCOL, UNSPECIFIED; STEARIC ACID; CROSCARMELLOSE SODIUM

192R - TARGET -DOC SOD 50 MG & SENNOSIDES 8.6 MG

ACTIVE INGREDIENTS

Each Tablet contains:

Docusate sodium 50 mg

Sennosides 8.6 mg

INACTIVE INGREDIENTS

INACTIVE INGREDIENTS: carnauba wax, colloidal silicon dioxide, croscarmellose sodium, dibasic calcium phosphate dihydrate, d-c yellow#10 aluminum lake, fd&c yellow#6 aluminum lake, Hypromellose, magnesium stearate, microcrystalline cellulose, polyethylene glycol, sodium benzoate, stearic acid, titanium dioxide

INDICATIONS AND USAGE

Relieves occasional constipation (irregularity); generally causes a bowel movement in 6-12 hours

PURPOSE

Stimulant Laxative and Stool Softener

DOSAGE AND ADMINISTRATION

Directions:

Take preferably at bedtime or as directed by a doctor. If you do not have a comfortable bowel movement by the second day, increase dose by one tablet (not to exceed maximum dosage) or decrease dose until you are comfortable.

Adults and children 12 years and older: - Starting dosage: 2 tablets once a day - Maximum dosage: 4 tablets twice a day

Children 6 to under 12 years: - Starting dosage: 1 tablet once a day-Maximum dosage: 2 tablets twice a day

Children 2 to under 6 years - Starting dosage: 1/2 tablet once a day- Maximum dosage: 1 tablet twice a day

Children under 2 years - Ask a doctor

WARNINGS

Do not use this product
If you are presently taking mineral oil unless directed by a doctor
Laxative products for longer than 1 week unless directed by a doctor

PREGNANT OR BREAST FEEDING

If pregnant or breastfeeding, ask a health professional before use.

Keep out of reach of children. In case of overdose, get medical help or contact a Poison Control Center right away.